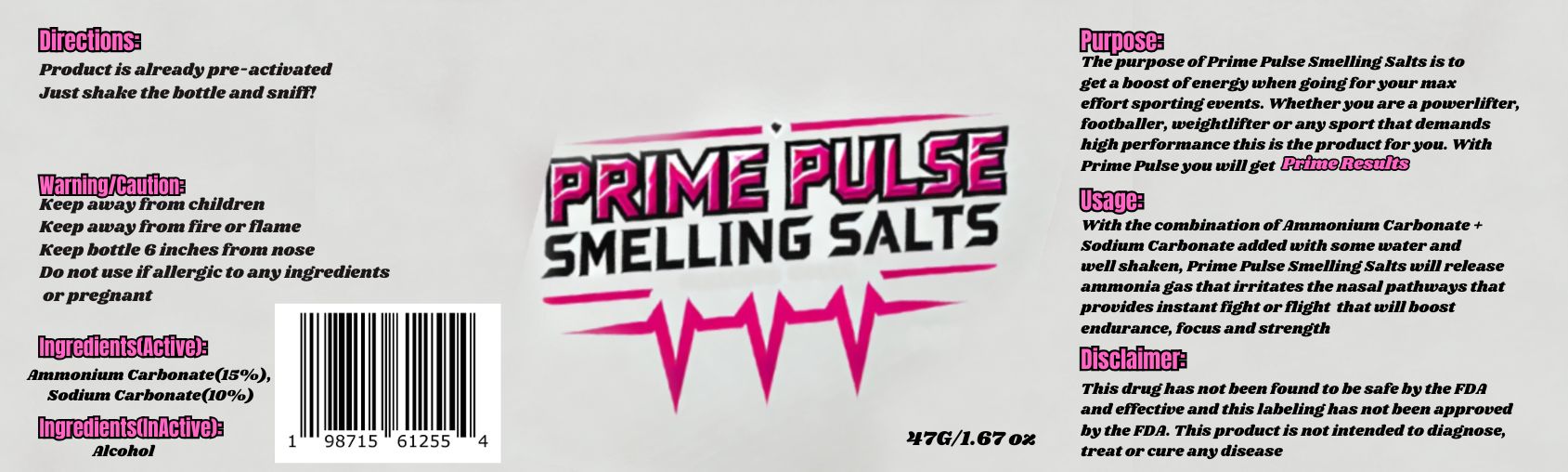 DRUG LABEL: PRIME PULSE SMELLING SALTS
NDC: 85813-002 | Form: GRANULE
Manufacturer: Direct Outlet Supplier LLC
Category: otc | Type: HUMAN OTC DRUG LABEL
Date: 20251126

ACTIVE INGREDIENTS: AMMONIUM CARBONATE 15 g/100 g; SODIUM CARBONATE 10 g/100 g
INACTIVE INGREDIENTS: ALCOHOL

PRIME PULSE SMELLING SALTS

Active Ingredients

Ammonium Carbonate................15%
Sodium Carbonate......................10%

Purpose

The purpose of Prime Pulse Smelling Salts is to get a boost of energy when going for your max effort sporting events. Whether you are a powerlifter, footballer, weightlifter or any sport that demands high performance this is the product for you. with Prime Pulse you will get Prime Results.

Usage

With the combination of Ammonium Carbonate + Sodium Carbonate added with some water and well shaken,Prime Pulse Smelling Salts will release ammonia gas that irritates the nasal pathways that provides instant fight or flight that will boosts endurance, focus and strength.

Warning and Precautions

Keep away from fire or flame

keep bottle 6 inches from nose.

Do not use if allergic to any ingredients or pregnant.

Directions

Product is already pre-activated. Just shake the bottle and sniff!

Inactive Ingredient

Alcohol

Disclaimer

This drug has not been found to be safe by the FDA and effective and this labeling has not been approved by the FDA. This product is not intended to diagnose, treat or cure any disease